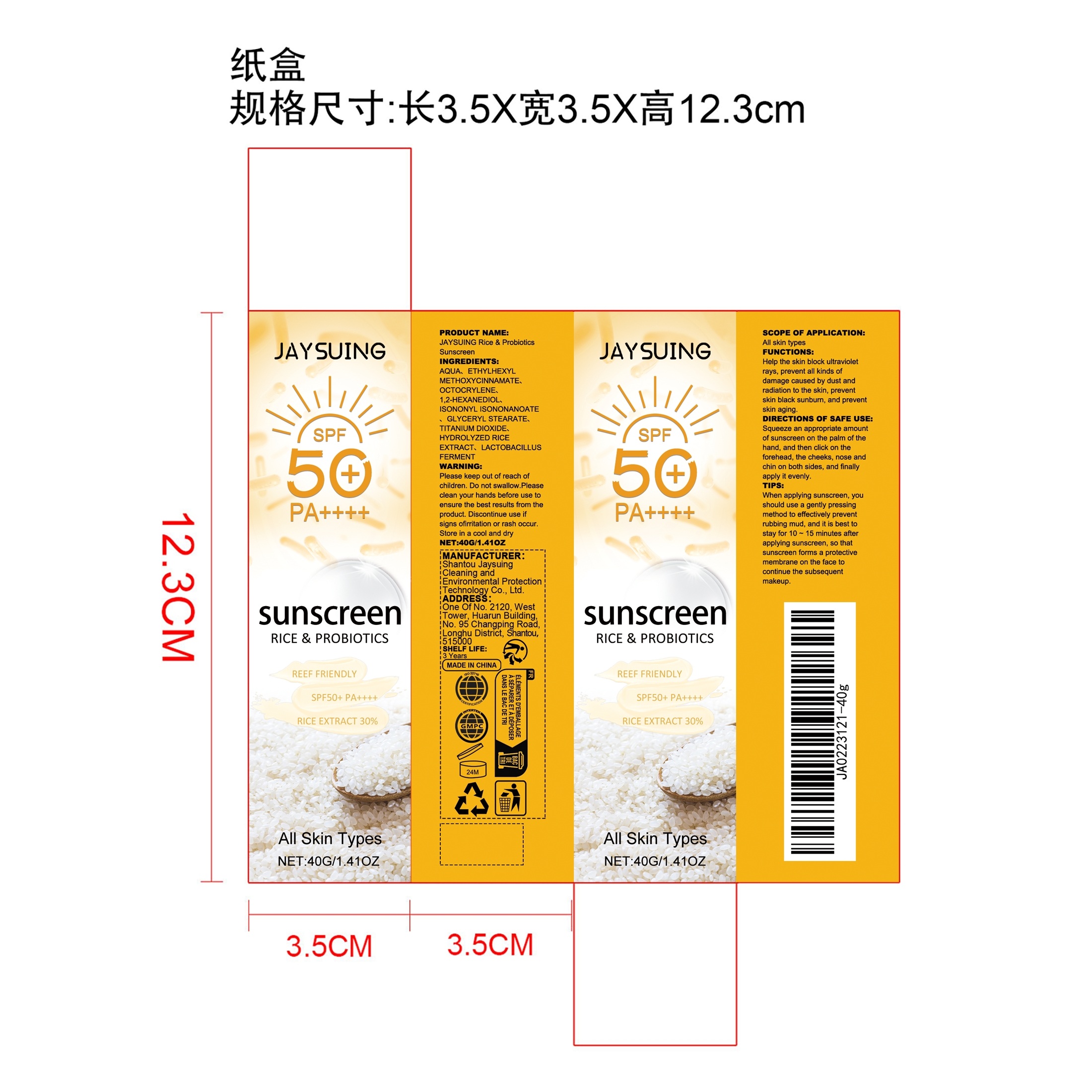 DRUG LABEL: JAYSUING Rice Probiotics Sunscreen
NDC: 85060-012 | Form: CREAM
Manufacturer: Shantou Jaysuing Cleaning and Environmental Protection Technology Co., Ltd.
Category: otc | Type: HUMAN OTC DRUG LABEL
Date: 20251212

ACTIVE INGREDIENTS: HYDROLYZED RICE PROTEIN (ENZYMATIC; 2000 MW) 0.008 mg/40 mg; LIMOSILACTOBACILLUS FERMENTUM 0.008 mg/40 mg
INACTIVE INGREDIENTS: TITANIUM DIOXIDE 0.4 mg/40 mg; ETHYLHEXYL METHOXYCINNAMATE 2 mg/40 mg; ISONONYL ISONONANOATE 1.6 mg/40 mg; OCTOCRYLENE 2 mg/40 mg; 1,2-HEXANEDIOL 0.12 mg/40 mg; AQUA 33.264 mg/40 mg; GLYCERYL STEARATE 0.6 mg/40 mg

ACTIVE INGREDIENT

HYDROLYZED RICE EXTRACT、LACTOBACILLUS FERMENT

PURPOSE

Help the skin block ultraviolet rays, prevent all kinds of damage caused by dust and radiation to the skin, prevent skin black sunburn, and prevent skin aging.

WHEN USING

Squeeze an appropriate amount of sunscreen on the palm of the hand, and then click on the forehead, the cheeks, nose and chin on both sides, and finally apply it evenly.

WARNINGS

Please keep out of reach of children. Do not swallow.Please clean your hands before use to ensure the best results from the product. Discontinue use if signs of irritation or rash occur. Store in a cool and dry place.

STOP USE

Discontinue use if signs of irritation or rash occur.

DO NOT USE

Discontinue use if signs of irritation or rash occur.

KEEP OUT OF REACH OF CHILDREN

Please keep out of reach of children. Do not swallow.

STORAGE AND HANDLING

Store in a cool and dry place.

INACTIVE INGREDIENT

AQUA、ETHYLHEXYL METHOXYCINNAMATE、OCTOCRYLENE、1,2-HEXANEDIOL、ISONONYL ISONONANOATE、GLYCERYL STEARATE、TITANIUM DIOXIDE

INDICATIONS AND USAGE

Squeeze an appropriate amount of sunscreen on the palm of the hand, and then click on the forehead, the cheeks, nose and chin on both sides, and finally apply it evenly.

DOSAGE AND ADMINISTRATION

Squeeze an appropriate amount of sunscreen on the palm of the hand, and then click on the forehead, the cheeks, nose and chin on both sides, and finally apply it evenly.